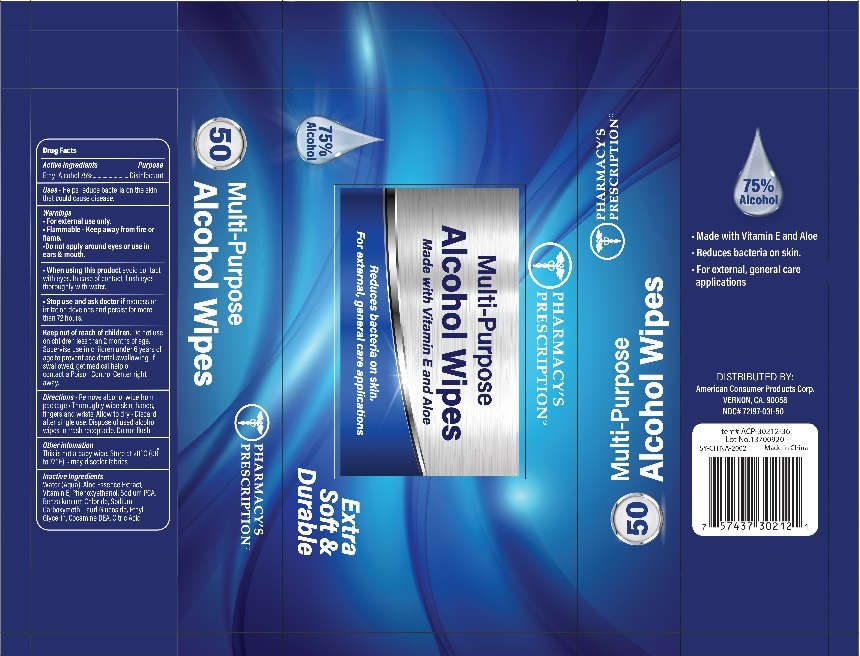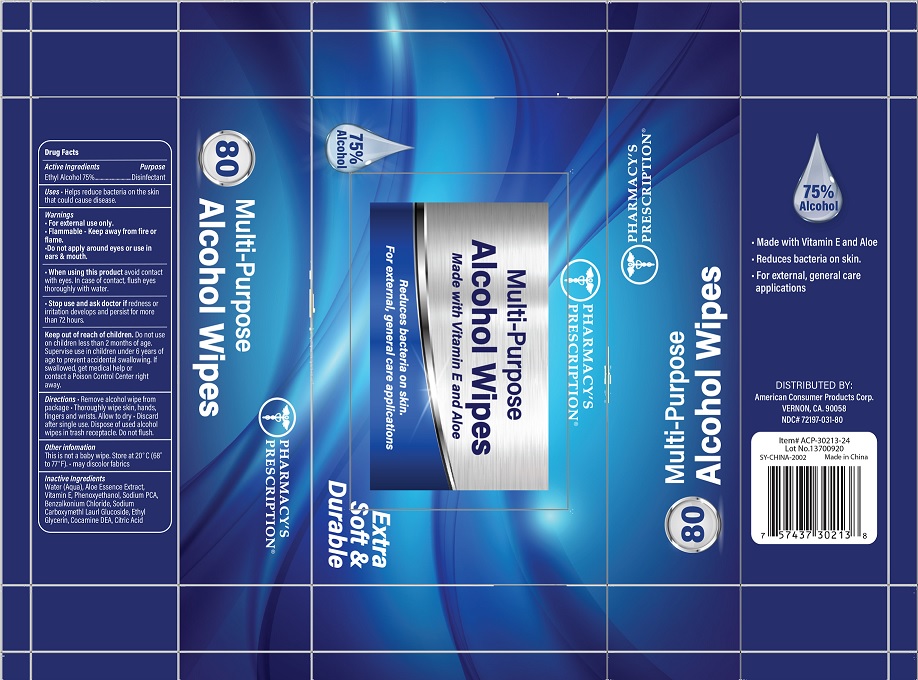 DRUG LABEL: Pharmacys Prescription Alcohol Wipes
NDC: 72197-031 | Form: SWAB
Manufacturer: American Consumer Products Corp
Category: otc | Type: HUMAN OTC DRUG LABEL
Date: 20200814

ACTIVE INGREDIENTS: ALCOHOL 75 mL/100 mL
INACTIVE INGREDIENTS: ALOE VERA LEAF; .ALPHA.-TOCOPHEROL ACETATE; PHENOXYETHANOL; ETHYL GLYCERIN ACETAL LEVULINATE; COCO DIETHANOLAMIDE; CITRIC ACID MONOHYDRATE; WATER; SODIUM PYRROLIDONE CARBOXYLATE; BENZALKONIUM CHLORIDE; LAURYL GLUCOSIDE

Pharmacys Prescription Wipes

Active Ingredient

Active Ingredients - Ethyl Alcohol 75%

Purpose

Disinfectant

Uses

Helps reduce bacteria on the skin that could cause disease.

Warnings

Warnings - For external use only.

Flammable - Keep away from fire or flame.

Do not apply around eyes or use in ears & mouth.

When using this product, avoid contact with eyes.

In case of contact, flush eyes thoroughly with water.

Stop use and ask a doctor

Strop use and ask doctor if redness or irritation develops and persists for more than 72 hours.

Keep out of reach of children. Do not use on children less than 2 months of age. Supervise use in children under 6 years of age to prevent accidental swallowing. If swallowed, get medical help or contact a Poison Control Center right away.

Directions

Directions - Remove alcohol wipe from package. Thouroughly wipe skin, hands, fingers and wrists. Allow to dry. Discard after single use. Dispose of used alcohol wipes in trash receptacle. Do not flush.

Other Information

Other information - this is not a baby wipe - store at 20°C (68° to 77°F).

- may discolor fabrics

INACTIVE INGREDIENTS

Water (Aqua), Aloe Essence Extract, Vitamin E, Phenoxyethanol, Sodium PCA, Benzalkonium Chloride, Sodium Carboxymethl Laurl Glucoside, Ethyl Glycerin, Cocamine DEA, Citric Acid

Distributed by

American Consumer Products Corp.

VERNON, CA 90058

Made in China